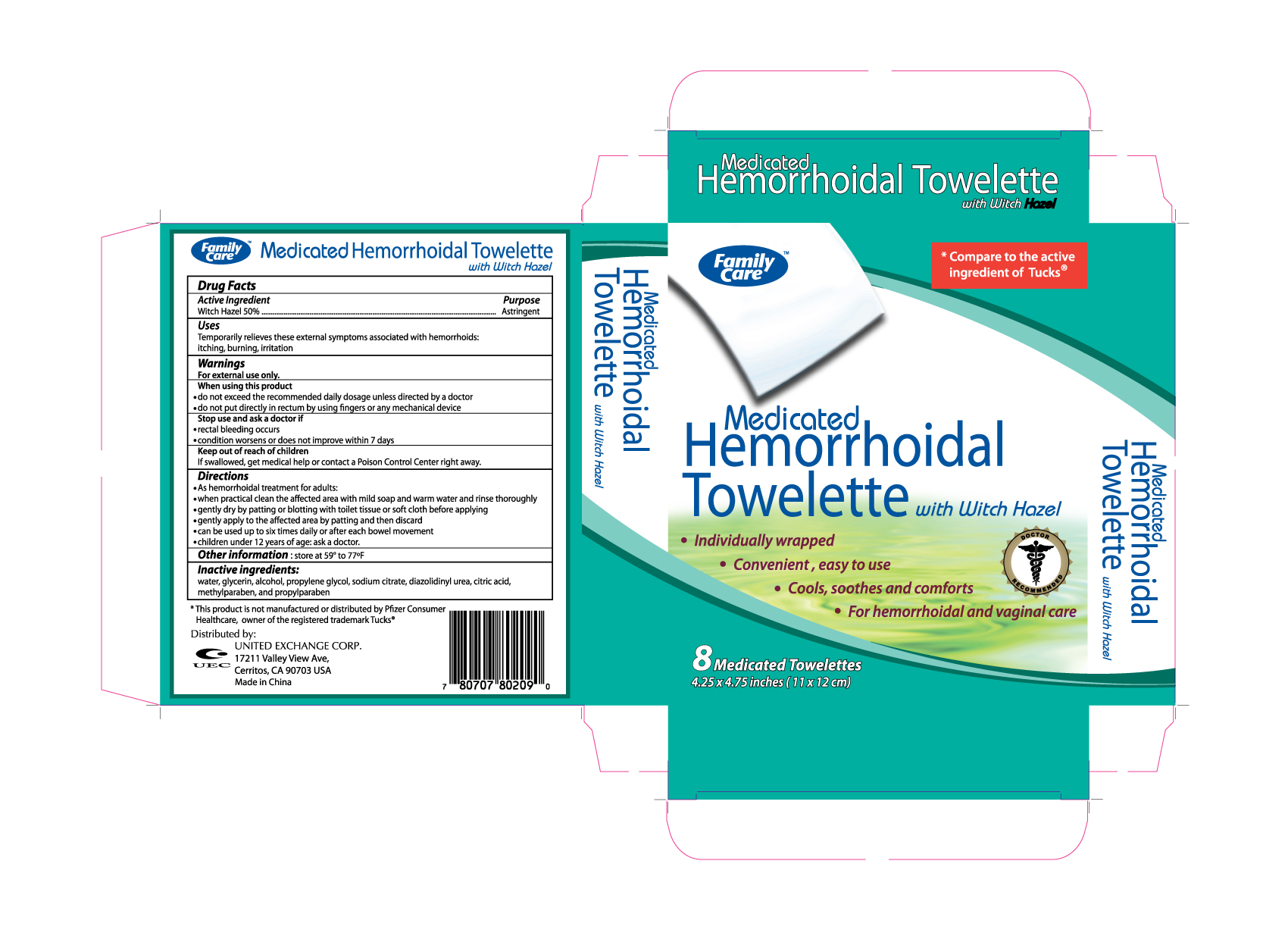 DRUG LABEL: FAMILY CARE MEDICATED HEMORRHOIDAL 
NDC: 65923-802 | Form: CLOTH
Manufacturer: UNITED EXCHANGE CORPORATION
Category: otc | Type: HUMAN OTC DRUG LABEL
Date: 20110720

ACTIVE INGREDIENTS: WITCH HAZEL 5 g/1 1
INACTIVE INGREDIENTS: WATER; GLYCERIN; ALCOHOL; PROPYLENE GLYCOL; SODIUM CITRATE; DIAZOLIDINYL UREA; CITRIC ACID MONOHYDRATE; METHYLPARABEN; PROPYLPARABEN

DRUG FACTS

Active Ingredient Purpose

Witch Hazel 50% .......................................................................................Astringent

Uses

Temporarily relieves these external symptoms associated with hemorrhoids: itching, burning, irritation

Warnings

For external use only.

When using this product

- do not exceed the recommended daily dosage unless directed by a doctor
- do not put directly in rectum by using fingers or any mechanical device

Stop use and ask a doctor if

- rectal bleeding occurs
- condition worsens or does not improve within 7 days

Keep out of reach of children

If swallowed, get medical help or contact a Poison Control Center right away.

Directions

- As hemorrhoidal treatment for adults:
- when practical clean the affected area with mild soap and warm water and rinse thoroughly
- gently dry by patting or blotting with toilet tissue or soft cloth before applying
- gently apply to the affected area by patting and then discard
- can be used up to six times daily or after each bowel movement
- children under 12 years of age: ask a doctor.

Other information: store at 59o to 77oF

Inactive ingredient:

water, glycerin, alcohol, propylene glycol, sodium citrate, diazolidinyl urea, citric acid, methylparaben, and propylparaben

DOSAGE AND ADMINISTRATION

Distributed by:

United Exchange Corp.

17211 Valley View Ave.

Cerritos, CA 90703 USA

Made in China

PACKAGE LABEL

Enter section text here